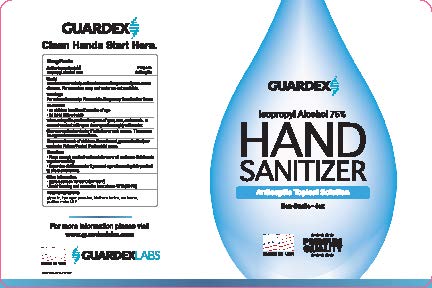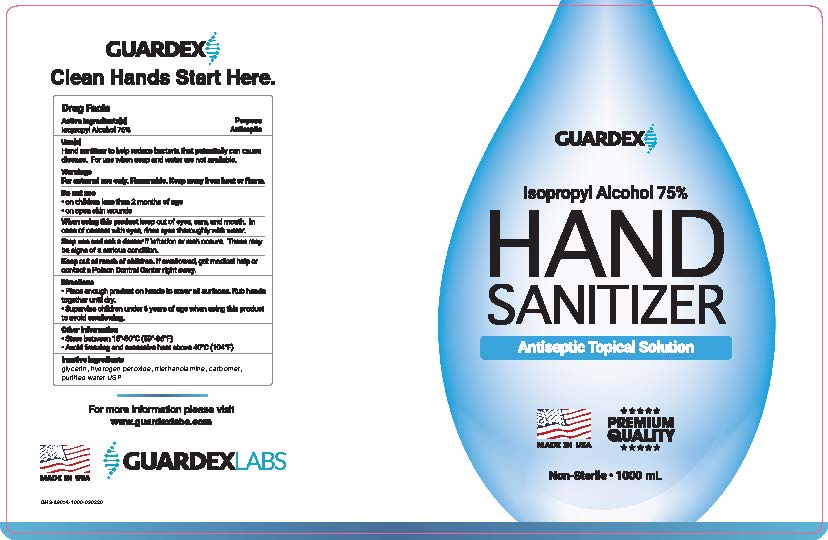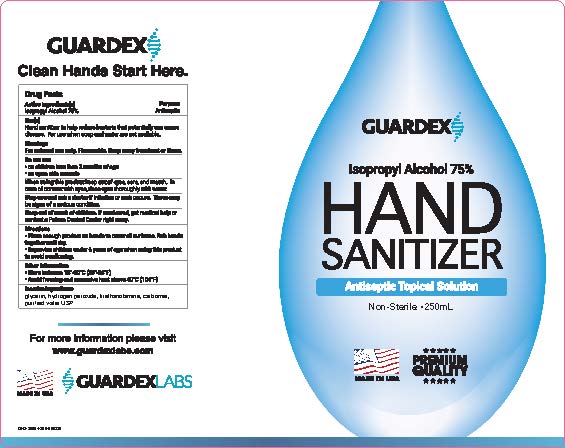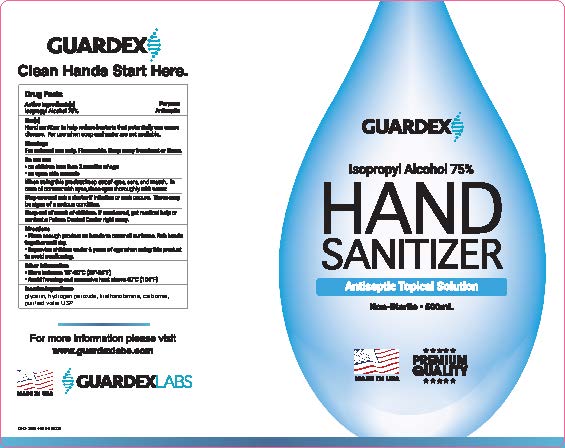 DRUG LABEL: Guardex Hand Sanitizer Antiseptic Solution
NDC: 80307-002 | Form: LIQUID
Manufacturer: Guardex Labs, Inc.
Category: otc | Type: HUMAN OTC DRUG LABEL
Date: 20200903

ACTIVE INGREDIENTS: ISOPROPYL ALCOHOL 187.5 mL/250 mL
INACTIVE INGREDIENTS: TRIETHANOLAMINE TRISTEARATE; HYDROGEN PEROXIDE; GLYCERIN; WATER; (3-BROMOPROPYL)BENZENE

Guardex Hand Sanitizer Antiseptic Topical Solution

Active Ingredient

Isopropyl Alcohol 75%

Purpose

Antiseptic

Uses

Hand Sanitizer to help reduce bacteria that potentially can cause disease. For use when soap and water are not available.

Warnings

For external use only. Flammable. Keep away from heat or flame.

Do not use

On children less than 2 months of age

On open skin wounds

When using this product

Keep out of eyes, ears and mouth. In case of contact with eyes, rinse eyes thoroughly with water.

Stop use and ask a doctor

If irritation or rash occurs. These may be signs of a serious condition.

Keep out of reach of children.

If swallowed, get medical help or contact a Poison Control Center right away.

Directions

Place enough product on hands to cover all surfaces.

Rub hands together until dry.

Supervise children under 6 years of age when using this product to avoid swallowing.

Other Information

-Store between 15-30C (59-86F).

-Avoid freezing and excessive heat above 40C (104F)

Inactive Ingredients

glycerin, hydrogen peroxide, Triethanolamine, carbomer, purified water USP